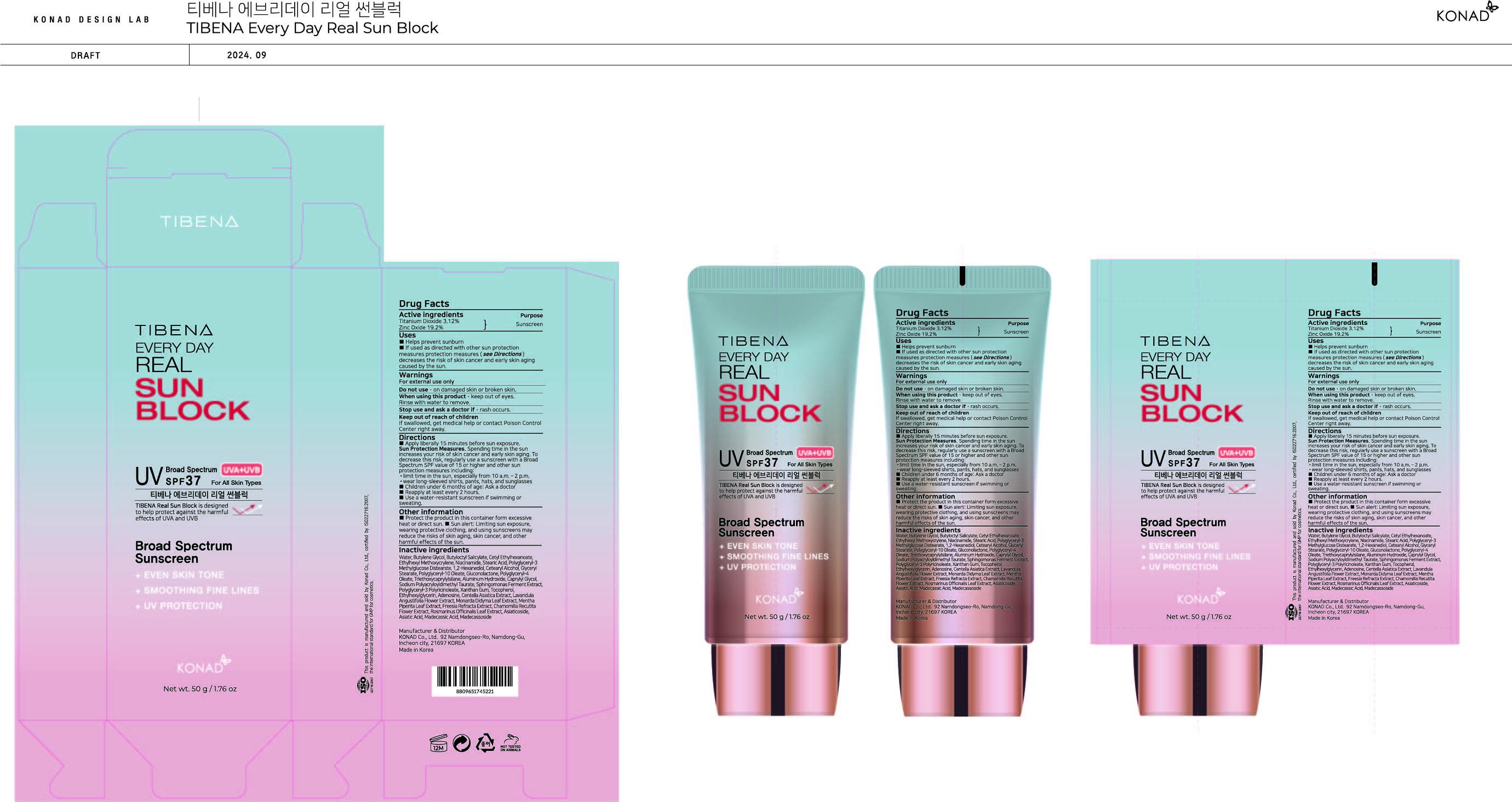 DRUG LABEL: TIBENA EVERY DAY REAL SUN BLOCK
NDC: 74740-450 | Form: CREAM
Manufacturer: KONAD CO LTD
Category: otc | Type: HUMAN OTC DRUG LABEL
Date: 20260226

ACTIVE INGREDIENTS: ZINC OXIDE 9.6 g/50 mL; TITANIUM DIOXIDE 1.56 g/50 mL
INACTIVE INGREDIENTS: CAPRYLYL GLYCOL; ADENOSINE; MADECASSIC ACID; BUTYLOCTYL SALICYLATE; BUTYLENE GLYCOL; POLYGLYCERYL-10 OLEATE; TRIETHOXYCAPRYLYLSILANE; SODIUM POLYACRYLOYLDIMETHYL TAURATE; GLYCERYL MONOSTEARATE; TOCOPHEROL; ROSEMARY; ALUMINUM HYDROXIDE; ASIATIC ACID; CENTELLA ASIATICA TRITERPENOIDS; CETYL ETHYLHEXANOATE; POLYGLYCERYL-3 METHYLGLUCOSE DISTEARATE; WATER; NIACINAMIDE; STEARIC ACID; CETOSTEARYL ALCOHOL; GLUCONOLACTONE; POLYGLYCERYL-4 OLEATE; XANTHAN GUM; MONARDA DIDYMA LEAF; ASIATICOSIDE; ETHYLHEXYL METHOXYCRYLENE; 1,2-HEXANEDIOL; ETHYLHEXYLGLYCERIN; MADECASSOSIDE

KONAD CO LTD_TIBENA EVERY DAY REAL SUN BLOCK

Active ingredients

Titanium Dioxide 3.12 %

Zinc Oxide 19.2 %

Purpose

sunscreen

Uses

• helps prevent sunburn

• if used as directed with other sun protection measures (see Directions) decreases the risk of skin cancer and early skin aging caused by the sun.

Warnings

For external use only

Do not use

· on damaged skin or broken skin.

When using this product

· keep out of eyes. Rinse with water to remove.

Stop use and ask a doctor if

· rash occurs.

Keep out of reach of children

If swallowed, get medical help or contact Poison Control Center right away.

Directions

■ Apply liberally 15 minutes before sun exposure.
Sun Protection Measures. Spending time in the sun increases your risk of skin cancer and early skin aging. To decrease this risk, regularly use a sunscreen with a Broad Spectrum SPF value of 15 or higher and other sun protection measures including:
·limit time in the sun, especially from 10 a.m. – 2 p.m.
·wear long-sleeved shirts, pants, hats, and sunglasses
■ Children under 6 months of age: Ask a doctor
■ Reapply at least every 2 hours.
■ Use a water-resistant sunscreen if swimming or sweating.

Other information

■ Protect the product in this container form excessive heat or direct sun. ■ Sun alert: Limiting sun exposure, wearing protective clothing, and using sunscreens may reduce the risks of skin aging, skin cancer, and other harmful effects of the sun.

Inactive ingredients

Water, Butylene Glycol, Butyloctyl Salicylate, Cetyl Ethylhexanoate, Ethylhexyl Methoxycrylene, Niacinamide, Stearic Acid, Polyglyceryl-3 Methylglucose Distearate, 1,2-Hexanediol, Cetearyl Alcohol, Glyceryl Stearate, Polyglyceryl-10 Oleate, Gluconolactone, Polyglyceryl-4 Oleate, Triethoxycaprylylsilane, Aluminum Hydroxide, Caprylyl Glycol, Sodium Polyacryloyldimethyl Taurate, Sphingomonas Ferment Extract, Polyglyceryl-3 Polyricinoleate, Xanthan Gum, Tocopherol, Ethylhexylglycerin, Adenosine, Centella asiatica Extract, Lavandula Angustifolia Flower Extract, Monarda Didyma Leaf Extract, Mentha Piperita Leaf Extract, Freesia Refracta Extract, Chamomilla Recutita Flower Extract, Rosmarinus Officinalis Leaf Extract, Asiaticoside, Asiatic acid, Madecassic acid, Madecassoside